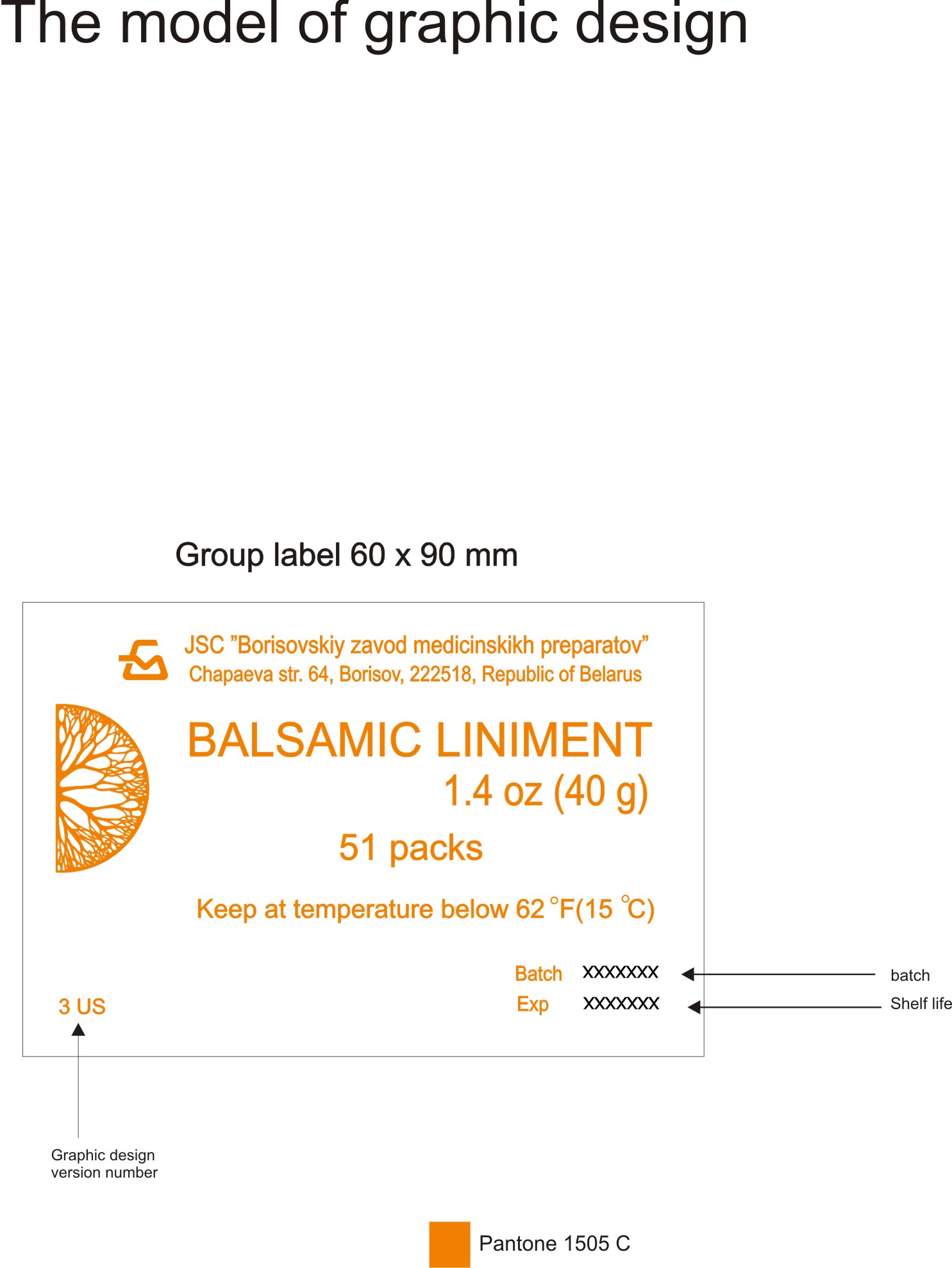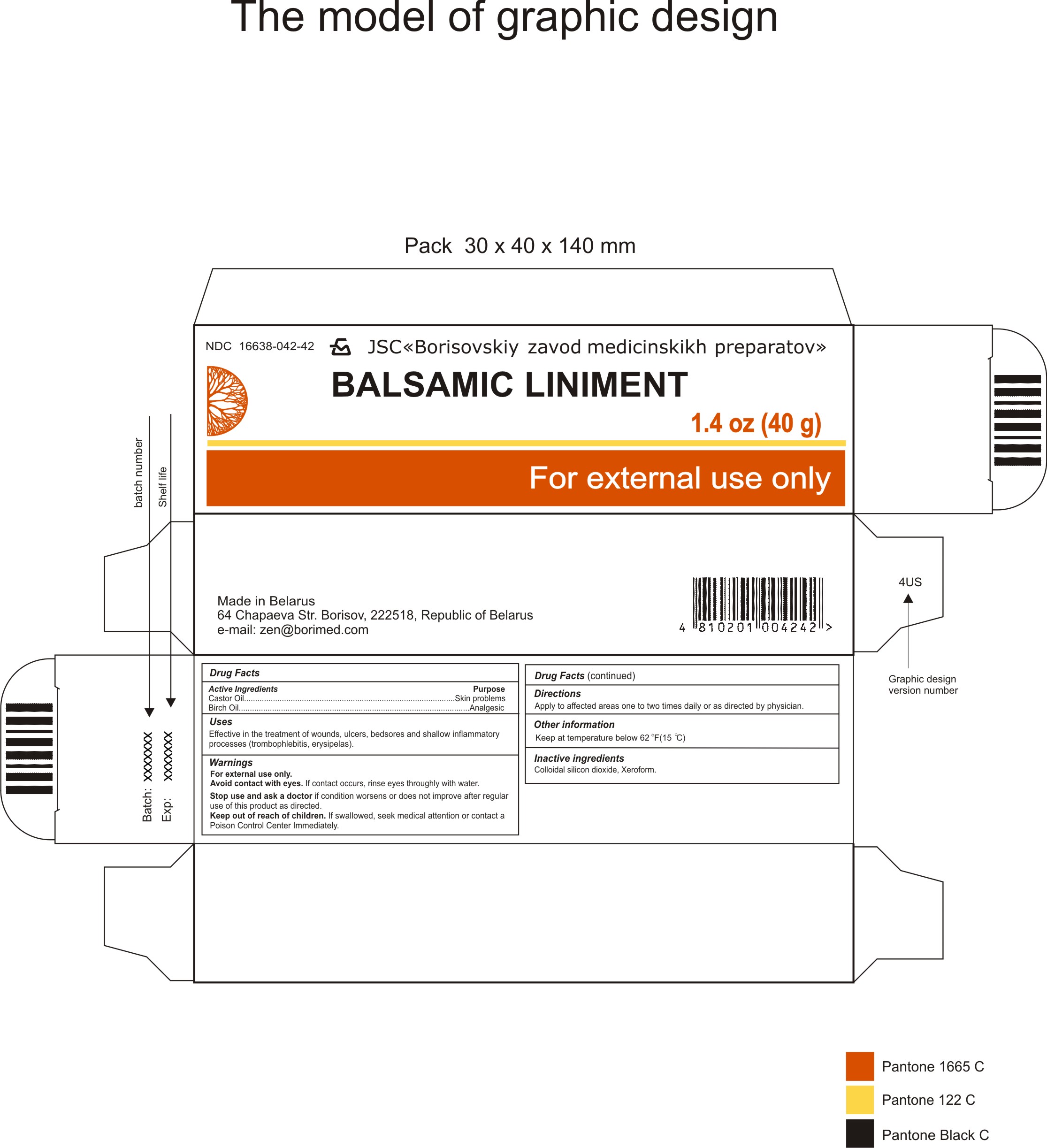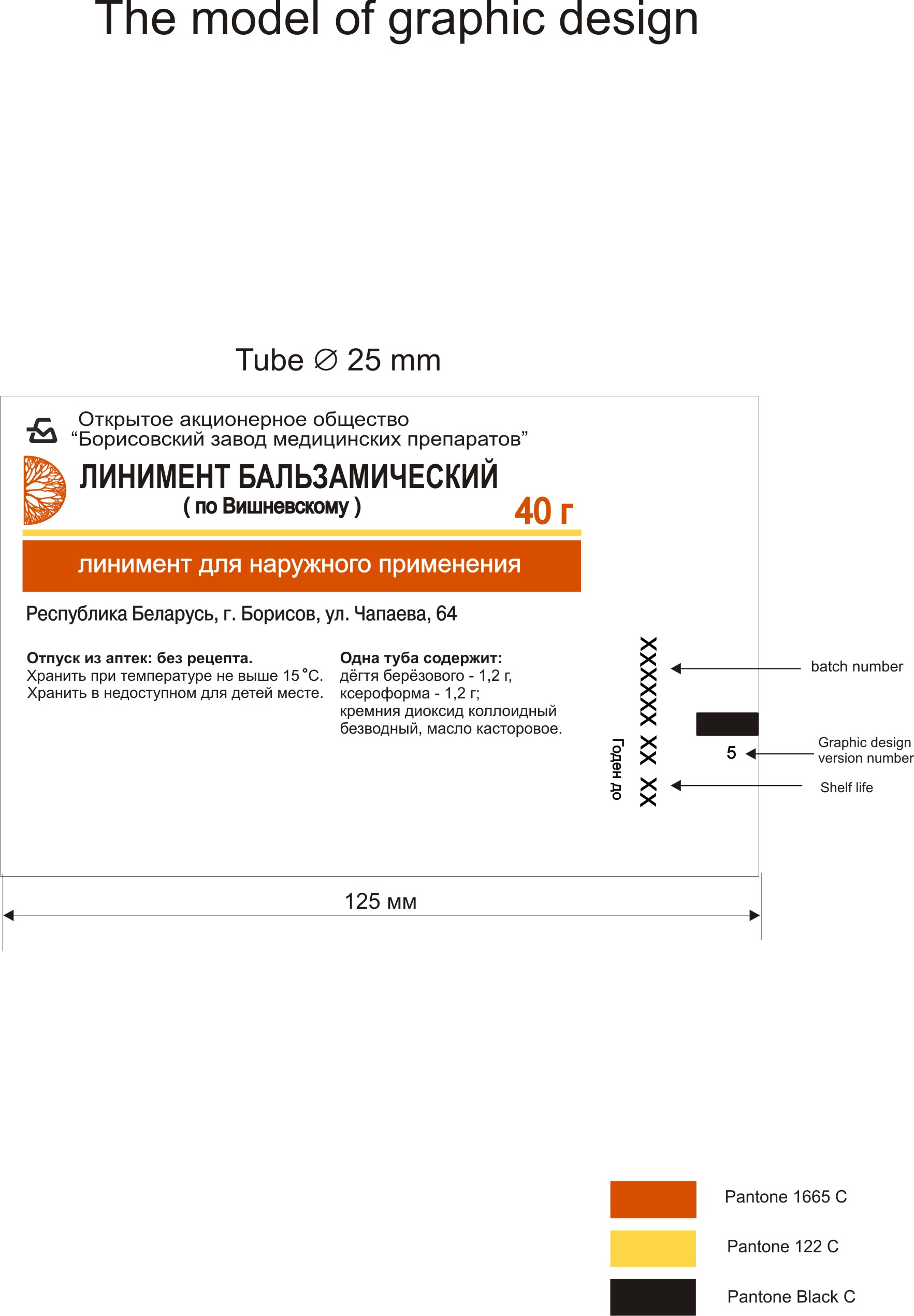 DRUG LABEL: Balsamic Liniment
NDC: 16638-042 | Form: LINIMENT
Manufacturer: Borisovskiy Zavod Medicinskikh Preparatov JSC
Category: otc | Type: HUMAN OTC DRUG LABEL
Date: 20151126

ACTIVE INGREDIENTS: CASTOR OIL 35.6 g/40 g; BETULA PENDULA TAR OIL 1.2 g/40 g
INACTIVE INGREDIENTS: COLLOIDAL SILICON DIOXIDE 2 g/40 g; BISMUTH TRIBROMOPHENATE 1.2 g/40 g

Drug facts

Active Ingredients

Castor Oil - 35.6 g, Birch Oil - 1.2 g

Purpose

Analgesic - dermatologicals

Uses

Effective in the treatment of wounds, ulcers, bedsores and shallow inflammatory processes (trombophlebitis, erysipelas).

Warnings

For external use only.

Avoid contact with eyes. If contact occurs, rinse eyes throughly with water.

Stop use and ask a doctor if condition worsens or does not improve after regular use of this product as directed.

Keep out of reach of children. If swallowed, seek medical attention or contact a Poison Control Center Immediately.

Directions

Apply to affected areas one to two times daily or as directed by physician.

Other information

Keep at temperature below 62oF (15 oC).

Inactive ingredients

Colloidal silicon dioxide, Xeroform.